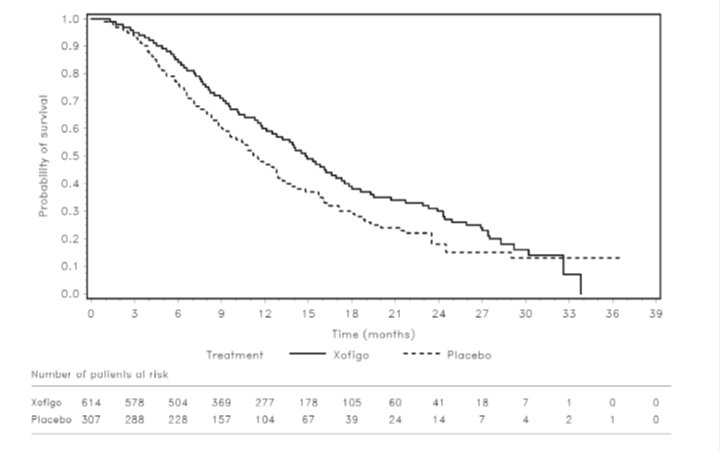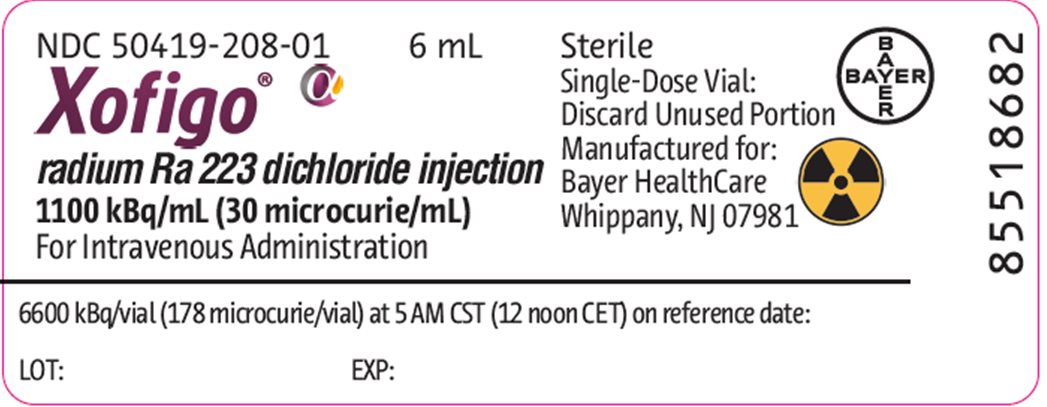 DRUG LABEL: Xofigo
NDC: 50419-208 | Form: INJECTION
Manufacturer: Bayer HealthCare Pharmaceuticals Inc.
Category: prescription | Type: HUMAN PRESCRIPTION DRUG LABEL
Date: 20191210

ACTIVE INGREDIENTS: RADIUM RA-223 DICHLORIDE 30 uCi/1 mL
INACTIVE INGREDIENTS: SODIUM CHLORIDE; SODIUM CITRATE, UNSPECIFIED FORM; HYDROCHLORIC ACID; WATER

HIGHLIGHTS OF PRESCRIBING INFORMATION

These highlights do not include all the information needed to use XOFIGO safely and effectively. See full prescribing information for XOFIGO.
XOFIGO (radium Ra 223 dichloride) injection, for intravenous use
Initial U.S. Approval: 2013

RECENT MAJOR CHANGES

Warnings and Precautions, Embryo-Fetal Toxicity (5.3) 12/2019

1 INDICATIONS AND USAGE

Xofigo is an alpha particle-emitting radioactive therapeutic agent indicated for the treatment of patients with castration-resistant prostate cancer, symptomatic bone metastases and no known visceral metastatic disease. (1)

2 DOSAGE AND ADMINISTRATION

The dose regimen of Xofigo is 55 kBq (1.49 microcurie) per kg body weight, given at 4 week intervals for 6 injections. (2.1)

3 DOSAGE FORMS AND STRENGTHS

Single-dose vial at a concentration of 1,100 kBq/mL (30 microcurie/mL) at the reference date with a total radioactivity of 6,600 kBq/vial (178 microcurie/vial) at the reference date. (3)

4 CONTRAINDICATIONS

None.

5 WARNINGS AND PRECAUTIONS

- Bone Marrow Suppression: Measure blood counts prior to treatment initiation and before every dose of Xofigo. Discontinue Xofigo if hematologic values do not recover within 6 to 8 weeks after treatment. Monitor patients with compromised bone marrow reserve closely. Discontinue Xofigo in patients who experience life-threatening complications despite supportive care measures. (5.1)
- Increased Fractures and Mortality in Combination with Abiraterone plus Prednisone/Prednisolone: Xofigo is not recommended in combination with abiraterone acetate plus prednisone/prednisolone. (5.2)
- Embryo-Fetal Toxicity: Xofigo can cause fetal harm. Advise males with female partners of reproductive potential to use effective contraception. (5.3, 8.1, 8.3)

6 ADVERSE REACTIONS

The most common adverse drug reactions (≥ 10%) in patients receiving Xofigo were nausea, diarrhea, vomiting, and peripheral edema.

The most common hematologic laboratory abnormalities (≥ 10%) were anemia, lymphocytopenia, leukopenia, thrombocytopenia, and neutropenia. (6.1)

To report SUSPECTED ADVERSE REACTIONS, contact Bayer HealthCare Pharmaceuticals Inc. at 1-888-842-2937 or FDA at 1-800-FDA-1088 or www.fda.gov/medwatch.

FULL PRESCRIBING INFORMATION

1 INDICATIONS AND USAGE

Xofigo is indicated for the treatment of patients with castration-resistant prostate cancer, symptomatic bone metastases and no known visceral metastatic disease.

2 DOSAGE AND ADMINISTRATION

2.1 Recommended Dosage

The dose regimen of Xofigo is 55 kBq (1.49 microcurie) per kg body weight, given at 4 week intervals for 6 injections. Safety and efficacy beyond 6 injections with Xofigo have not been studied.

The volume to be administered to a given patient should be calculated using the:

- Patient’s body weight (kg)
- Dosage level 55 kBq/kg body weight or 1.49 microcurie/kg body weight
- Radioactivity concentration of the product (1,100 kBq/mL; 30 microcurie/mL) at the reference date
- Decay correction factor to correct for physical decay of radium-223.

The total volume to be administered to a patient is calculated as follows:

Volume to be administered (mL) | = | Body weight in kg × 55 kBq/kg body weight
Volume to be administered (mL) | = | Decay factor × 1,100 kBq/mL

or

Volume to be administered (mL) | = | Body weight in kg × 1.49 microcurie/kg body weight
Volume to be administered (mL) | = | Decay factor × 30 microcurie/mL

Table 1: Decay Correction Factor Table
Days from Reference Date | Decay Factor | Days from Reference Date | Decay Factor
-14 | 2.296 | 0 | 0.982
-13 | 2.161 | 1 | 0.925
-12 | 2.034 | 2 | 0.870
-11 | 1.914 | 3 | 0.819
-10 | 1.802 | 4 | 0.771
-9 | 1.696 | 5 | 0.725
-8 | 1.596 | 6 | 0.683
-7 | 1.502 | 7 | 0.643
-6 | 1.414 | 8 | 0.605
-5 | 1.330 | 9 | 0.569
-4 | 1.252 | 10 | 0.536
-3 | 1.178 | 11 | 0.504
-2 | 1.109 | 12 | 0.475
-1 | 1.044 | 13 | 0.447
 |  | 14 | 0.420
The Decay Correction Factor Table is corrected to 12 noon Central Standard Time (CST). To determine the decay correction factor, count the number of days before or after the reference date. The Decay Correction Factor Table includes a correction to account for the 7 hour time difference between 12 noon Central European Time (CET) at the site of manufacture and 12 noon US CST, which is 7 hours earlier than CET.

Immediately before and after administration, the net patient dose of administered Xofigo should be determined by measurement in an appropriate radioisotope dose calibrator that has been calibrated with a National Institute of Standards and Technology (NIST) traceable radium-223 standard (available upon request from Bayer) and corrected for decay using the date and time of calibration. The dose calibrator must be calibrated with nationally recognized standards, carried out at the time of commissioning, after any maintenance procedure that could affect the dosimetry and at intervals not to exceed one year.

2.2 Administration

Administer Xofigo by slow intravenous injection over 1 minute.

Flush the intravenous access line or cannula with isotonic saline before and after injection of Xofigo.

Discard any unused portion, if applicable [see Dosage and Administration (2.3)].

2.3 Instructions for Use/Handling

General warning

Xofigo (an alpha particle-emitting pharmaceutical) should be received, used and administered only by authorized persons in designated clinical settings. The receipt, storage, use, transfer and disposal of Xofigo are subject to the regulations and/or appropriate licenses of the competent official organization.

Xofigo should be handled by the user in a manner which satisfies both radiation safety and pharmaceutical quality requirements. Appropriate aseptic precautions should be taken.

Radiation protection

The administration of Xofigo is associated with potential risks to other persons (e.g., medical staff, caregivers and patient’s household members) from radiation or contamination from spills of bodily fluids such as urine, feces, or vomit. Therefore, radiation protection precautions must be taken in accordance with national and local regulations.^1

For drug handling

Follow the normal working procedures for the handling of radiopharmaceuticals and use universal precautions for handling and administration such as gloves and barrier gowns when handling blood and bodily fluids to avoid contamination. In case of contact with skin or eyes, the affected area should be flushed immediately with water. In the event of spillage of Xofigo, the local radiation safety officer should be contacted immediately to initiate the necessary measurements and required procedures to decontaminate the area. A complexing agent such as 0.01 M ethylene-diamine-tetraacetic acid (EDTA) solution is recommended to remove contamination.

For patient care

Whenever possible, patients should use a toilet and the toilet should be flushed several times after each use. When handling bodily fluids, simply wearing gloves and hand washing will protect caregivers. Clothing soiled with Xofigo or patient fecal matter or urine should be washed promptly and separately from other clothing.

Radium-223 is primarily an alpha emitter, with a 95.3% fraction of energy emitted as alpha-particles. The fraction emitted as beta-particles is 3.6%, and the fraction emitted as gamma-radiation is 1.1%. The external radiation exposure associated with handling of patient doses is expected to be low, because the typical treatment activity will be below 8,000 kBq (216 microcurie). In keeping with the As Low As Reasonably Achievable (ALARA) principle for minimization of radiation exposure, it is recommended to minimize the time spent in radiation areas, to maximize the distance to radiation sources, and to use adequate shielding. Any unused product or materials used in connection with the preparation or administration are to be treated as radioactive waste and should be disposed of in accordance with local regulations.

The gamma radiation associated with the decay of radium-223 and its daughters allows for the radioactivity measurement of Xofigo and the detection of contamination with standard instruments.

Instructions for preparation

Parenteral drug products should be inspected visually for particulate matter and discoloration prior to administration, whenever solution and container permit.

Xofigo is a ready-to-use solution and should not be diluted or mixed with any solutions. Each vial is for single use only.

Dosimetry

The absorbed radiation doses in major organs were calculated based on clinical biodistribution data in five patients with castration-resistant prostate cancer. Calculations of absorbed radiation doses were performed using OLINDA/EXM (Organ Level INternal Dose Assessment/EXponential Modeling), a software program based on the Medical Internal Radiation Dose (MIRD) algorithm, which is widely used for established beta and gamma emitting radionuclides. For radium-223, which is primarily an alpha particle-emitter, assumptions were made for intestine, red marrow and bone/osteogenic cells to provide the best possible absorbed radiation dose calculations for Xofigo, considering its observed biodistribution and specific characteristics. Additional particular modeling was applied for the lungs. The absorbed dose to the lungs is estimated as the dose contribution from 223Ra and daughter decays in the blood-containing fraction of the lung mass and also the dose contribution from 219Rn and daughter decays in the respiratory tract.

The calculated absorbed radiation doses to different organs per administered activity are listed in Table 2. The organs with highest absorbed radiation doses are bone (osteogenic cells), red marrow, and large intestine walls. The absorbed doses to other organs are lower.

Table 2: Absorbed Radiation Doses per Administered Activity
Organ | Mean (mGy/MBq) | Mean (rad/mCi) | Coefficient of Variation (%)
Osteogenic cells | 1152 | 4263 | 41
Red marrow | 139 | 514 | 41
LLI wall [LLI: lower large intestine; ULI: upper large intestine; colon dose = 0.57 × ULI dose + 0.43 × LLI dose2] | 46 | 172 | 83
Colon | 38 | 142 | 56
ULI wall | 32 | 120 | 50
Small intestine wall | 7.3 | 27 | 45
Urinary bladder wall | 4.0 | 15 | 63
Kidneys | 3.2 | 12 | 36
Liver | 3.0 | 11 | 36
Heart wall | 1.7 | 6.4 | 42
Lungs | 1.2 | 4.5 | 48
Ovaries | 0.49 | 1.8 | 40
Uterus | 0.26 | 0.94 | 28
Gallbladder wall | 0.23 | 0.85 | 14
Stomach wall | 0.14 | 0.51 | 22
Adrenals | 0.12 | 0.44 | 56
Muscle | 0.12 | 0.44 | 41
Pancreas | 0.11 | 0.41 | 43
Brain | 0.10 | 0.37 | 80
Spleen | 0.09 | 0.33 | 54
Testes | 0.08 | 0.31 | 59
Skin | 0.07 | 0.27 | 79
Thyroid | 0.07 | 0.26 | 96
Thymus | 0.06 | 0.21 | 109
Breasts | 0.05 | 0.18 | 120
Whole Body | 23 | 86 | 16

3 DOSAGE FORMS AND STRENGTHS

Xofigo (radium Ra 223 dichloride injection) is available in single-dose vials containing 6 mL of clear, colorless solution at a concentration of 1,100 kBq/mL (30 microcurie/mL) at the reference date with a total radioactivity of 6,600 kBq/vial (178 microcurie/vial) at the referencedate.

4 CONTRAINDICATIONS

None.

5 WARNINGS AND PRECAUTIONS

5.1 Bone Marrow Suppression

In the randomized trial, 2% of patients on the Xofigo arm experienced bone marrow failure or ongoing pancytopenia compared to no patients treated with placebo. There were two deaths due to bone marrow failure and for 7 of 13 patients treated with Xofigo, bone marrow failure was ongoing at the time of death. Among the 13 patients who experienced bone marrow failure, 54% required blood transfusions. Four percent (4%) of patients on the Xofigo arm and 2% on the placebo arm permanently discontinued therapy due to bone marrow suppression.

In the randomized trial, deaths related to vascular hemorrhage in association with myelosuppression were observed in 1% of Xofigo-treated patients compared to 0.3% of patients treated with placebo. The incidence of infection-related deaths (2%), serious infections (10%), and febrile neutropenia (<1%) were similar for patients treated with Xofigo and placebo. Myelosuppression; notably thrombocytopenia, neutropenia, pancytopenia, and leukopenia; has been reported in patients treated with Xofigo. In the randomized trial, complete blood counts (CBCs) were obtained every 4 weeks prior to each dose and the nadir CBCs and times of recovery were not well characterized. In a separate single-dose phase 1 study of Xofigo, neutrophil and platelet count nadirs occurred 2 to 3 weeks after Xofigo administration at doses that were up to 1 to 5 times the recommended dose, and most patients recovered approximately 6 to 8 weeks after administration [see Adverse Reactions (6)].

Hematologic evaluation of patients must be performed at baseline and prior to every dose of Xofigo. Before the first administration of Xofigo, the absolute neutrophil count (ANC) should be ≥ 1.5 x 10^9/L, the platelet count ≥ 100 x 10^9/L and hemoglobin ≥ 10 g/dL. Before subsequent administrations of Xofigo, the ANC should be ≥ 1 x 10^9/L and the platelet count ≥ 50 x 10^9/L. If there is no recovery to these values within 6 to 8 weeks after the last administration of Xofigo, despite receiving supportive care, further treatment with Xofigo should be discontinued. Patients with evidence of compromised bone marrow reserve should be monitored closely and provided with supportive care measures when clinically indicated. Discontinue Xofigo in patients who experience life-threatening complications despite supportive care for bone marrow failure.

The safety and efficacy of concomitant chemotherapy with Xofigo have not been established. Outside of a clinical trial, concomitant use with chemotherapy is not recommended due to the potential for additive myelosuppression. If chemotherapy, other systemic radioisotopes or hemibody external radiotherapy are administered during the treatment period, Xofigo should be discontinued.

5.2 Increased Fractures and Mortality in Combination with Abiraterone plus Prednisone/Prednisolone

Xofigo is not recommended for use in combination with abiraterone acetate plus prednisone/prednisolone outside of clinical trials.

The clinical efficacy and safety of concurrent initiation of Xofigo treatment and abiraterone acetate plus prednisone/prednisolone treatment was assessed in a randomized, placebo-controlled multicenter phase 3 study (ERA-223 trial) in 806 patients with asymptomatic or mildly symptomatic castration resistant prostate cancer with bone metastases. The study was unblinded early based on an Independent Data Monitoring Committee recommendation.

At the primary analysis, an increased incidence of fractures (28.6% vs 11.4%) and deaths (38.5% vs 35.5%) have been observed in patients who received Xofigo in combination with abiraterone acetate plus prednisone/prednisolone compared to patients who received placebo in combination with abiraterone acetate plus prednisone/prednisolone. Safety and efficacy with the combination of Xofigo and agents other than gonadotropin-releasing hormone analogues have not been established.

-167640120650005.3 Embryo-Fetal Toxicity

The safety and efficacy of Xofigo have not been established in females. Based on its mechanism of action, Xofigo can cause fetal harm when administered to a pregnant female. Advise pregnant females and females of reproductive potential of the potential risk to a fetus. Advise male patients to use condoms and their female partners of reproductive potential to use effective contraception during and for 6 months after completing treatment with Xofigo [see Use in Specific Populations (8.1, 8.3) and Clinical Pharmacology (12.1)].

6 ADVERSE REACTIONS

The following serious adverse reactions are discussed in greater detail in another section of the label:

- Bone Marrow Suppression [see Warnings and Precautions (5.1)]

6.1 Clinical Trials Experience

Because clinical trials are conducted under widely varying conditions, adverse reaction rates observed in the clinical trials of a drug cannot be directly compared to rates in the clinical trials of another drug and may not reflect the rates observed in practice.

In the randomized clinical trial in patients with metastatic castration-resistant prostate cancer with bone metastases, 600 patients received intravenous injections of 55 kBq/kg (1.49 microcurie/kg) of Xofigo and best standard of care and 301 patients received placebo and best standard of care once every 4 weeks for up to 6 injections. Prior to randomization, 58% and 57% of patients had received docetaxel in the Xofigo and placebo arms, respectively. The median duration of treatment was 20 weeks (6 cycles) for Xofigo and 18 weeks (5 cycles) for placebo.

The most common adverse reactions (≥ 10%) in patients receiving Xofigo were nausea, diarrhea, vomiting, and peripheral edema (Table 3). Grade 3 and 4 adverse events were reported among 57% of Xofigo-treated patients and 63% of placebo-treated patients. The most common hematologic laboratory abnormalities in Xofigo-treated patients (≥ 10%) were anemia, lymphocytopenia, leukopenia, thrombocytopenia, and neutropenia (Table 4).

Treatment discontinuations due to adverse events occurred in 17% of patients who received Xofigo and 21% of patients who received placebo. The most common hematologic laboratory abnormalities leading to discontinuation for Xofigo were anemia (2%) and thrombocytopenia (2%).

Table 3 shows adverse reactions occurring in ≥ 2% of patients and for which the incidence for Xofigo exceeds the incidence for placebo.

Table 3: Adverse Reactions in the Randomized Trial
System/Organ Class Preferred Term | Xofigo (n=600) |  | Placebo (n=301)
System/Organ Class Preferred Term | Grades 1-4 % | Grades 3-4 % | Grades 1-4 % | Grades 3-4 %
Blood and lymphatic system disorders
Pancytopenia | 2 | 1 | 0 | 0
Gastrointestinal disorders
Nausea | 36 | 2 | 35 | 2
Diarrhea | 25 | 2 | 15 | 2
Vomiting | 19 | 2 | 14 | 2
General disorders and administration site conditions
Peripheral edema | 13 | 2 | 10 | 1
Renal and urinary disorders
Renal failure and impairment | 3 | 1 | 1 | 1

Laboratory Abnormalities

Table 4 shows hematologic laboratory abnormalities occurring in > 10% of patients and for which the incidence for Xofigo exceeds the incidence for placebo.

Table 4: Hematologic Laboratory Abnormalities
Hematologic Laboratory Abnormalities | Xofigo (n=600) |  | Placebo (n=301)
Hematologic Laboratory Abnormalities | Grades 1-4 % | Grades 3-4 % | Grades 1-4 % | Grades 3-4 %
Anemia | 93 | 6 | 88 | 6
Lymphocytopenia | 72 | 20 | 53 | 7
Leukopenia | 35 | 3 | 10 | <1
Thrombocytopenia | 31 | 3 | 22 | <1
Neutropenia | 18 | 2 | 5 | <1
Laboratory values were obtained at baseline and prior to each 4-week cycle.

As an adverse reaction, grade 3-4 thrombocytopenia was reported in 6% of patients on Xofigo and in 2% of patients on placebo. Among patients who received Xofigo, the laboratory abnormality grade 3-4 thrombocytopenia occurred in 1% of docetaxel naïve patients and in 4% of patients who had received prior docetaxel. Grade 3-4 neutropenia occurred in 1% of docetaxel naïve patients and in 3% of patients who have received prior docetaxel.

Fluid Status

Dehydration occurred in 3% of patients on Xofigo and 1% of patients on placebo. Xofigo increases adverse reactions such as diarrhea, nausea, and vomiting which may result in dehydration. Monitor patients’ oral intake and fluid status carefully and promptly treat patients who display signs or symptoms of dehydration or hypovolemia.

Injection Site Reactions

Erythema, pain, and edema at the injection site were reported in 1% of patients on Xofigo.

Secondary Malignant Neoplasms

Xofigo contributes to a patient’s overall long-term cumulative radiation exposure. Long-term cumulative radiation exposure may be associated with an increased risk of cancer and hereditary defects. Due to its mechanism of action and neoplastic changes, including osteosarcomas, in rats following administration of radium-223 dichloride, Xofigo may increase the risk of osteosarcoma or other secondary malignant neoplasms [see Nonclinical Toxicology (13.1)]. However, the overall incidence of new malignancies in the randomized trial was lower on the Xofigo arm compared to placebo (<1% vs. 2%; respectively), but the expected latency period for the development of secondary malignancies exceeds the duration of follow up for patients on the trial.

Subsequent Treatment with Cytotoxic Chemotherapy

In the randomized clinical trial, 16% patients in the Xofigo group and 18% patients in the placebo group received cytotoxic chemotherapy after completion of study treatments. Adequate safety monitoring and laboratory testing was not performed to assess how patients treated with Xofigo will tolerate subsequent cytotoxic chemotherapy.

7 DRUG INTERACTIONS

No formal clinical drug interaction studies have been performed.

Subgroup analyses indicated that the concurrent use of bisphosphonates or calcium channel blockers did not affect the safety and efficacy of Xofigo in the randomized clinical trial.

8 USE IN SPECIFIC POPULATIONS

8.1 Pregnancy

Risk Summary

The safety and efficacy of Xofigo have not been established in females. Based on mechanism of action, Xofigo can cause fetal harm when administered to a pregnant female [see Clinical Pharmacology (12.1)]. While there are no human or animal data on the use of Xofigo in pregnancy, maternal use of a radioactive therapeutic agent could affect development of a fetus. Advise pregnant females and females of reproductive potential of the potential risk to a fetus.

8.2 Lactation

Risk Summary

The safety and efficacy of Xofigo have not been established in females. There is no data on the presence of radium-223 dichloride in human milk, the effects on the breastfed child, or the effects on milk production.

8.3 Females and Males of Reproductive Potential

Contraception

Males

Because of potential effects on spermatogenesis associated with radiation, advise male patients to use condoms and their female partners of reproductive potential to use effective contraception during and for 6 months after completing treatment with Xofigo [see Use in Specific Populations (8.1)].

Infertility

Males

Based on mechanism of action, Xofigo may impair fertility in males of reproductive potential [see Clinical Pharmacology (12.1) and Nonclinical Toxicology (13.1)].

8.4 Pediatric Use

The safety and efficacy of Xofigo in pediatric patients have not been established.

In single- and repeat-dose toxicity studies in rats, findings in the bones (depletion of osteocytes, osteoblasts, osteoclasts, fibro-osseous lesions, disruption/disorganization of the physis/growth line) and teeth (missing, irregular growth, fibro-osseous lesions in bone socket) correlated with a reduction of osteogenesis that occurred at clinically relevant doses beginning in the range of 22 – 88 kBq (0.59 - 2.38 microcurie) per kg body weight.

8.5 Geriatric Use

Of the 600 patients treated with Xofigo in the randomized trial, 75% were 65 years of age and over and while 33% were 75 years of age and over. No dosage adjustment is considered necessary in elderly patients. No overall differences in safety or effectiveness were observed between these subjects and younger subjects, and other reported clinical experience has not identified differences in responses between the elderly and younger patients, but greater sensitivity of some older individuals cannot be ruled out.

8.6 Patients with Hepatic Impairment

No dedicated hepatic impairment trial for Xofigo has been conducted. Since radium-223 is neither metabolized by the liver nor eliminated via the bile, hepatic impairment is unlikely to affect the pharmacokinetics of radium-223 dichloride [see Clinical Pharmacology (12.3)]. Based on subgroup analyses in the randomized clinical trial, dose adjustment is not needed in patients with mild hepatic impairment. No dose adjustments can be recommended for patients with moderate or severe hepatic impairment due to lack of clinical data.

8.7 Patients with Renal Impairment

No dedicated renal impairment trial for Xofigo has been conducted. Based on subgroup analyses in the randomized clinical trial, dose adjustment is not needed in patients with existing mild (creatinine clearance [CrCl] 60 to 89 mL/min) or moderate (CrCl 30 to 59 mL/min) renal impairment. No dose adjustment can be recommended for patients with severe renal impairment (CrCl less than 30 mL/min) due to limited data available (n = 2) [see Clinical Pharmacology (12.3)].

10 OVERDOSAGE

There have been no reports of inadvertent overdosing of Xofigo during clinical studies.

There is no specific antidote. In the event of an inadvertent overdose of Xofigo, utilize general supportive measures, including monitoring for potential hematological and gastrointestinal toxicity, and consider using medical countermeasures such as aluminum hydroxide, barium sulfate, calcium carbonate, calcium gluconate, calcium phosphate, or sodium alginate.^1

Single Xofigo doses up to 276 kBq (7.46 microcurie) per kg body weight were evaluated in a phase 1 clinical trial and no dose-limiting toxicities were observed.

11 DESCRIPTION

Radium Ra 223 dichloride, an alpha particle-emitting pharmaceutical, is a radiotherapeutic drug.

Xofigo is supplied as a clear, colorless, isotonic, and sterile solution to be administered intravenously with pH between 6 and 8.

Each milliliter of solution contains 1,100 kBq radium-223 dichloride (30 microcurie), corresponding to 0.58 ng radium-223, at the reference date. Radium is present in the solution as a free divalent cation.

Each vial contains 6 mL of solution (6,600 kBq (178 microcurie) radium-223 dichloride at the reference date). The inactive ingredients are 6.3 mg/mL sodium chloride USP (tonicity agent), 7.2 mg/mL sodium citrate USP (for pH adjustment), 0.2 mg/mL hydrochloric acid USP (for pH adjustment), and water for injection USP.

The molecular weight of radium-223 dichloride, ^223RaCl2, is 293.9 g/mol.

Radium-223 has a half-life of 11.4 days. The specific activity of radium-223 is 1.9 MBq (51.4 microcurie)/ng.

The six-stage-decay of radium-223 to stable lead-207 occurs via short-lived daughters, and is accompanied predominantly by alpha emissions. There are also beta and gamma emissions with different energies and emission probabilities. The fraction of energy emitted from radium-223 and its daughters as alpha-particles is 95.3% (energy range of 5 - 7.5 MeV). The fraction emitted as beta-particles is 3.6% (average energies are 0.445 MeV and 0.492 MeV), and the fraction emitted as gamma-radiation is 1.1% (energy range of 0.01 - 1.27 MeV).

12 CLINICAL PHARMACOLOGY

12.1 Mechanism of Action

The active moiety of Xofigo is the alpha particle-emitting isotope radium-223 (as radium Ra 223 dichloride), which mimics calcium and forms complexes with the bone mineral hydroxyapatite at areas of increased bone turnover, such as bone metastases (see Table 2). The high linear energy transfer of alpha particles (80 keV/micrometer) leads to a high frequency of double-strand DNA breaks in adjacent cells including tumor cells, osteoblasts and osteoclasts, resulting in an anti-tumor effect on bone metastases. The alpha particle range from radium-223 dichloride is less than 100 micrometers (less than 10 cell diameters) which limits damage to the surrounding normal tissue.

12.2 Pharmacodynamics

Compared with placebo, there was a difference in favor of Xofigo for all five serum biomarkers for bone turnover studied in a phase 2 randomized study (bone formation markers: bone alkaline phosphatase [ALP], total ALP and procollagen I N propeptide [PINP], bone resorption markers: C-terminal crosslinking telopeptide of type I collagen [S-CTX-I] and type I collagen crosslinked C-telopeptide [ICTP]).

12.3 Pharmacokinetics

The pharmacokinetics of radium-223 dichloride in blood was linear in terms of dose proportionality and time independence in the dose range investigated (51 to 276 kBq [1.38 to 7.46 microcurie] per kg body weight).

Distribution

After intravenous injection, radium-223 is rapidly cleared from the blood and is distributed primarily into bone or is excreted into intestine. Fifteen minutes post-injection, about 20% of the injected radioactivity remained in blood. At 4 hours, about 4% of the injected radioactivity remained in blood, decreasing to less than 1% at 24 hours after the injection. At 10 minutes post-injection, radioactivity was observed in bone and in intestine. At 4 hours post-injection, the percentage of the radioactive dose present in bone and intestine was approximately 61% and 49%, respectively. No significant uptake was seen in other organs such as heart, liver, kidneys, urinary bladder, and spleen at 4 hours post-injection [see Dosage and Administration (2.3)].

Metabolism

Radium-223 is an isotope that decays and is not metabolized.

Elimination

The whole body measurements indicated that approximately 63% of the administered radioactivity was excreted from the body within 7 days after injection (after correcting for decay). Fecal excretion is the major route of elimination from the body. At 48 hours after injection, the cumulative fecal excretion was 13% (range 0 - 34%), and the cumulative urine excretion was 2% (range 1 - 5%). There was no evidence of hepato-biliary excretion based on imaging data.

The rate of elimination of radium-223 dichloride from the gastrointestinal tract is influenced by the high variability in intestinal transit rates across the population. Patients with a slower intestinal transit rate could potentially receive a higher intestinal radiation exposure. It is not known whether this will result in increased gastrointestinal toxicity.

Special Populations

Pediatric patients

Safety and effectiveness of Xofigo have not been established in children and adolescents below 18 years of age.

Patients with hepatic impairment

No dedicated pharmacokinetic study in patients with hepatic impairment has been conducted. However, since radium-223 is not metabolized and there is no evidence of hepato-biliary excretion based on imaging data, hepatic impairment is not expected to affect the pharmacokinetics of radium-223 dichloride.

Patients with renal impairment

No dedicated pharmacokinetic study in patients with renal impairment has been conducted. However, since excretion in urine is minimal and the major route of elimination is via the feces, renal impairment is not expected to affect the pharmacokinetics of radium-223 dichloride.

12.6 Cardiac Electrophysiology

The effect of a single dose of 55 kBq/kg of radium-223 dichloride on the QTc interval was evaluated in a subgroup of 29 patients (21 received Xofigo and 8 received placebo) in the randomized clinical trial. No large changes in the mean QTc interval (i.e., greater than 20 ms) were detected up to 6 hours post-dose. The potential for delayed effects on the QT interval after 6 hours was not evaluated.

13 NONCLINICAL TOXICOLOGY

13.1 Carcinogenesis, Mutagenesis, Impairment of Fertility

Animal studies have not been conducted to evaluate the carcinogenic potential of radium-223 dichloride. However, in repeat-dose toxicity studies in rats, osteosarcomas, a known effect of bone-seeking radionuclides, were observed at clinically relevant doses 7 to 12 months after the start of treatment. The presence of other neoplastic changes, including lymphoma and mammary gland carcinoma, was also reported in 12- to 15-month repeat-dose toxicity studies in rats.

Genetic toxicology studies have not been conducted with radium-223 dichloride. However, the mechanism of action of radium-223 dichloride involves induction of double-strand DNA breaks, which is a known effect of radiation.

Animal studies have not been conducted to evaluate the effects of radium-223 dichloride on male or female fertility or reproductive function. Xofigo may impair fertility and reproductive function in humans based on its mechanism of action.

14 CLINICAL STUDIES

The efficacy and safety of Xofigo were evaluated in a double-blind, randomized, placebo-controlled phase 3 clinical trial of patients with castration-resistant prostate cancer with symptomatic bone metastases. Patients with visceral metastases and malignant lymphadenopathy exceeding 3 cm were excluded. The primary efficacy endpoint was overall survival. A key secondary efficacy endpoint was time to first symptomatic skeletal event (SSE) defined as external beam radiation therapy (EBRT) to relieve skeletal symptoms, new symptomatic pathologic bone fracture, occurrence of spinal cord compression, or tumor-related orthopedic surgical intervention. There were no scheduled radiographic assessments performed on study. All patients were to continue androgen deprivation therapy. At the cut-off date of the pre-planned interim analysis, a total of 809 patients had been randomized 2:1 to receive Xofigo 55 kBq (1.49 microcurie)/kg intravenously every 4 weeks for 6 cycles (n = 541) plus best standard of care or matching placebo plus best standard of care (n = 268). Best standard of care included local EBRT, corticosteroids, antiandrogens, estrogens, estramustine or ketoconazole. Therapy was continued until unacceptable toxicity or initiation of cytotoxic chemotherapy, other systemic radioisotope, hemi-body EBRT or other investigational drug. Patients with Crohn’s disease, ulcerative colitis, prior hemibody radiation or untreated imminent spinal cord compression were excluded from the study. In patients with bone fractures, orthopedic stabilization was performed before starting or resuming treatment with Xofigo.

The following patient demographics and baseline disease characteristics were balanced between the arms. The median age was 71 (range 44-94) with a racial distribution of 94% Caucasian, 4% Asian, 2% Black and <1% Other. Patients were enrolled predominantly from Europe (85%) with 4% of patients enrolled from North America. ECOG performance status was 0-1 in 86% of patients. Eighty-five percent of patients had 6 or more bone scan lesions and of those 40% had > 20 lesions or a superscan. Opiate pain medications were used for cancer-related pain in 54% of patients, non-opiate pain medications in 44% of patients and no pain medications in 2% of patients. Patients were stratified by baseline ALP, bisphosphonate use, and prior docetaxel exposure. Prior bisphosphonates were used by 41% of patients and 58% had received prior docetaxel. During the treatment period, 83% of Xofigo patients and 82% of placebo patients received gonadotropin-releasing hormone agonists and 21% of Xofigo patients and 34% of placebo patients received concomitant antiandrogens. Use of systemic steroids (41%) and bisphosphonates (40%) was balanced between the arms.

The pre-specified interim analysis of overall survival revealed a statistically significant improvement in patients receiving XOFIGO plus best standard of care compared with patients receiving placebo plus best standard of care. An exploratory updated overall survival analysis performed before patient crossover with an additional 214 events resulted in findings consistent with the interim analysis (Table 5).

Table 5: Overall Survival Results from the Phase 3 Clinical Trial
 | Xofigo | Placebo
Interim Analysis
Subjects randomized | 541 | 268
Number of deaths | 191 (35.3%) | 123 (45.9%)
Censored | 350 (64.7%) | 145 (54.1%)
Median survival (months) [Survival time is calculated as months from date of randomization to date of death from any cause. Subjects who are not deceased at time of analysis are censored on the last date subject was known to be alive or lost to follow-up.]; (95% CI) | 14.0; (12.1, 15.8) | 11.2; (9.0, 13.2)
p-value [p-value is from a log-rank test stratified by total ALP, current use of bisphosphonates, and prior use of docetaxel.] | 0.00185
Hazard ratio (95% CI) [Hazard ratio is from a Cox proportional hazards model adjusted for total ALP, current use of bisphosphonates, and prior use of docetaxel. Hazard ratio < 1 favors radium-223 dichloride.] | 0.695 (0.552, 0.875)
Updated Analysis
Subjects randomized | 614 | 307
Number of deaths | 333 (54.2%) | 195 (63.5%)
Censored | 281 (45.8%) | 112 (36.5%)
Median survival (months); (95% CI) | 14.9; (13.9, 16.1) | 11.3; (10.4, 12.8)
Hazard ratio (95% CI) | 0.695 (0.581, 0.832)

The Kaplan-Meier curves for overall survival based on the updated survival results are shown in Figure 1.

Figure 1: Kaplan-Meier Overall Survival Curves from the Phase 3 Clinical Trial

The survival results were supported by a delay in the time to first SSE favoring the Xofigo arm. The majority of events consisted of external beam radiotherapy to bone metastases.

15 REFERENCES

1. Radiation Emergency Medical Management. [REMM/National Library of Medicine Website.] http://www.remm.nlm.gov/int_contamination.htm#blockingagents
2. International Commission on Radiological Protection, ICRP Publication 128, 2015. http://www.icrp.org/publication.asp?id=ICRP Publication 128

16 HOW SUPPLIED/STORAGE AND HANDLING

Xofigo (radium Ra 223 dichloride injection) is supplied in single-dose vials containing 6 mL of clear, colorless solution at a concentration of 1,100 kBq/mL (30 microcurie/mL) with a total radioactivity of 6,600 kBq/vial (178 microcurie/vial) at the reference date (NDC 50419-208-01).

Store at room temperature, below 40° C (104° F). Store Xofigo in the original container or equivalent radiation shielding.

This preparation is approved for use by persons under license by the Nuclear Regulatory Commission or the relevant regulatory authority of an Agreement State.

Follow procedures for proper handling and disposal of radioactive pharmaceuticals [see Dosage and Administration (2.3)].

17 PATIENT COUNSELING INFORMATION

Bone Marrow Suppression
Increased Fractures and Mortality in Combination with Abiraterone plus Prednisone/Prednisolone
Fluid Status
Instructions for Use/Handling
Embryo-Fetal Toxicity
Infertility

- Advise patients to be compliant with blood cell count monitoring appointments while receiving Xofigo. Explain the importance of routine blood cell counts. Instruct patients to report signs of bleeding or infections [see Warnings and Precautions (5.1)].
  Increased Fractures and Mortality in Combination with Abiraterone plus Prednisone/Prednisolone
- Advise patients that Xofigo had increased bone fractures and mortality when used in combination with abiraterone acetate and prednisone/prednisolone. Inform patients to speak with their healthcare provider about any other medications they are currently taking for prostate cancer [see Warnings and Precautions (5.2)].
  Fluid Status
- Advise patients to stay well hydrated and to monitor oral intake, fluid status, and urine output while being treated with Xofigo. Instruct patients to report signs of dehydration, hypovolemia, urinary retention, or renal failure / insufficiency [see Adverse Reactions (6.1)].
  Instructions for Use/Handling
- Inform patients that there are no restrictions regarding personal contact (visual or physical proximity) with other people after receiving Xofigo. Advise patients to follow good hygiene practices while receiving Xofigo and for at least 1 week after the last injection in order to minimize radiation exposure from bodily fluids to household members and caregivers. Whenever possible, patients should use a toilet and the toilet should be flushed several times after each use. Clothing soiled with patient fecal matter or urine should be washed promptly and separately from other clothing. Caregivers should use universal precautions for patient care such as gloves and barrier gowns when handling bodily fluids to avoid contamination. When handling bodily fluids, wearing gloves and hand washing will protect caregivers [see Dosage and Administration (2.3)].
  Embryo-Fetal Toxicity
- Advise male patients to use condoms and their female partners of reproductive potential to use effective contraception during and for 6 months following completion of Xofigo treatment [see Use in Specific Populations (8.1, 8.3)].
  Infertility
- Inform male patients that Xofigo may impair fertility [see Use in Specific Populations (8.3)].

Manufactured for:

Bayer HealthCare Pharmaceuticals Inc.
Whippany, NJ 07981

Xofigo is a trademark of Bayer Aktiengesellschaft.

© 2013, Bayer HealthCare Pharmaceuticals Inc.
All rights reserved.

PACKAGE LABEL

NDC 50419-208-01

6 mL

Xofigo®

radium Ra 223 dichloride injection

1100 kBq/mL (30 microcurie/mL)

For Intravenous Administration

Sterile

Single-Dose Vial:

Discard Unused Portion

Manufactured for:

Bayer HealthCare
Whippany, NJ 07981

6600 kBq/vial (178 microcurie/vial) at 5AM CST (12 noon CET) on reference date:

LOT:

EXP: